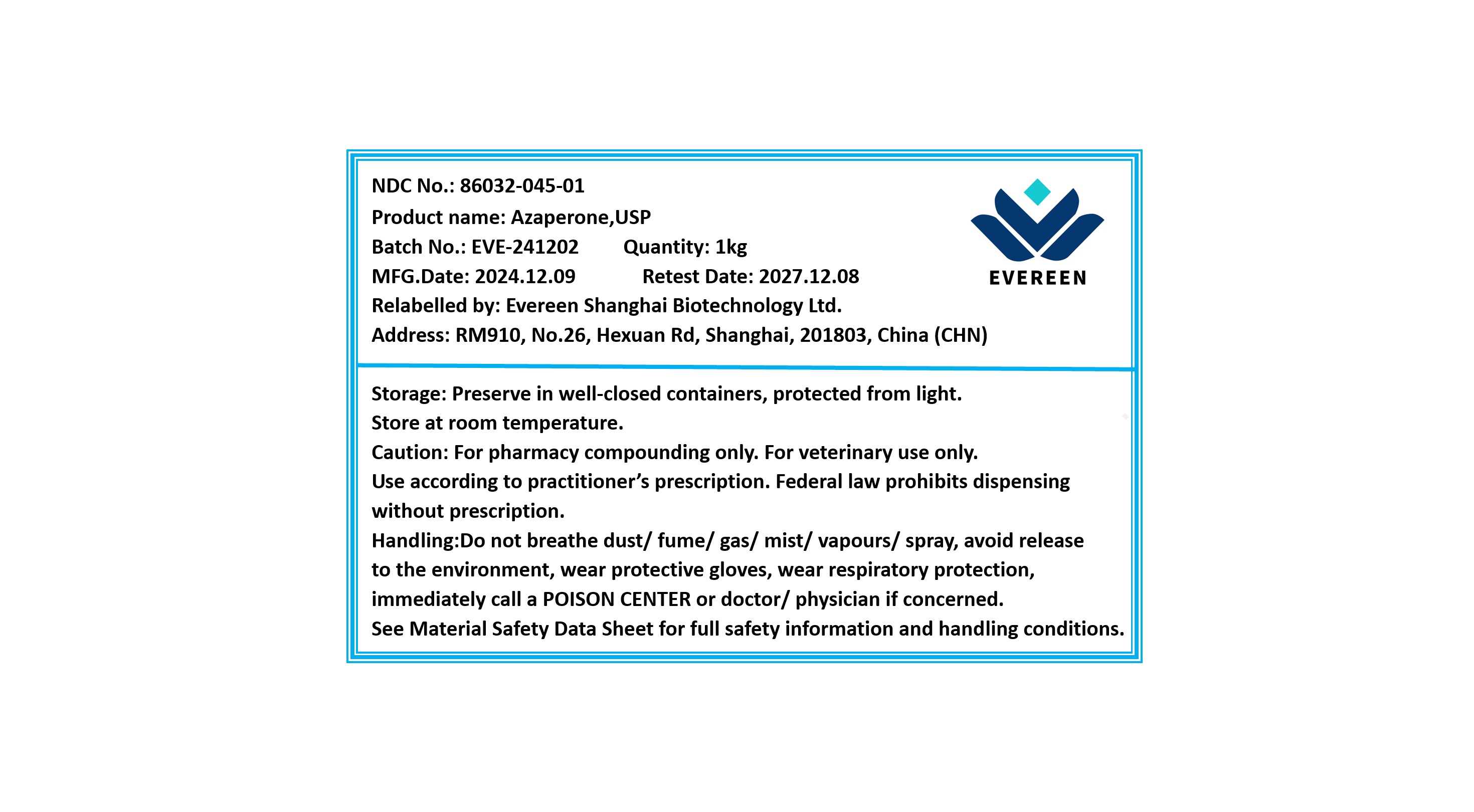 DRUG LABEL: Azaperone
NDC: 86032-045 | Form: POWDER
Manufacturer: Evereen Shanghai Biotechnology Ltd.
Category: other | Type: BULK INGREDIENT - ANIMAL DRUG
Date: 20250318

ACTIVE INGREDIENTS: AZAPERONE 1 kg/1 kg

Azaperone